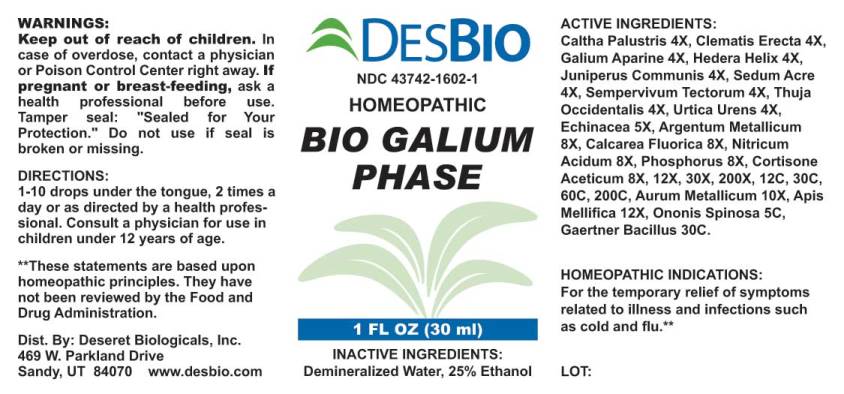 DRUG LABEL: Bio Galium Phase
NDC: 43742-1602 | Form: LIQUID
Manufacturer: Deseret Biologicals, Inc.
Category: homeopathic | Type: HUMAN OTC DRUG LABEL
Date: 20240815

ACTIVE INGREDIENTS: CALTHA PALUSTRIS 4 [hp_X]/1 mL; CLEMATIS RECTA FLOWERING TOP 4 [hp_X]/1 mL; GALIUM APARINE 4 [hp_X]/1 mL; HEDERA HELIX FLOWERING TWIG 4 [hp_X]/1 mL; JUNIPER BERRY 4 [hp_X]/1 mL; SEDUM ACRE 4 [hp_X]/1 mL; SEMPERVIVUM TECTORUM LEAF 4 [hp_X]/1 mL; THUJA OCCIDENTALIS LEAFY TWIG 4 [hp_X]/1 mL; URTICA URENS 4 [hp_X]/1 mL; ECHINACEA ANGUSTIFOLIA 5 [hp_X]/1 mL; SILVER 8 [hp_X]/1 mL; CALCIUM FLUORIDE 8 [hp_X]/1 mL; NITRIC ACID 8 [hp_X]/1 mL; PHOSPHORUS 8 [hp_X]/1 mL; CORTISONE ACETATE 8 [hp_X]/1 mL; GOLD 10 [hp_X]/1 mL; APIS MELLIFERA 12 [hp_X]/1 mL; ONONIS SPINOSA WHOLE 5 [hp_C]/1 mL; SALMONELLA ENTERICA ENTERICA SEROVAR ENTERITIDIS 30 [hp_C]/1 mL
INACTIVE INGREDIENTS: WATER; ALCOHOL

Drug Facts:

ACTIVE INGREDIENTS:

Caltha Palustris 4X, Clematis Erecta 4X, Galium Aparine 4X, Hedera Helix 4X, Juniperus Communis 4X, Sedum Acre 4X, Sempervivum Tectorum 4X, Thuja Occidentalis 4X, Urtica Urens 4X, Echinacea (Angustifolia) 5X, Argentum Metallicum 8X, Calcarea Fluorica 8X, Nitricum Acidum 8X, Phosphorus 8X, Cortisone Aceticum 8X, 12X, 30X, 200X, 12C, 30C, 60C, 200C, Aurum Metallicum 10X, Apis Mellifica 12X, Ononis Spinosa 5C, Gaertner Bacillus (Bach) 30C.

HOMEOPATHIC INDICATIONS:

For the temporary relief of symptoms related to illness and infections such as cold and flu.**

**These statements are based upon homeopathic principles. They have not been reviewed by the Food and Drug Administration.

WARNINGS:

Keep out of reach of children. In case of overdose, contact a physician or Poison Control Center right away.

If pregnant or breast-feeding, ask a health professional before use.

Tamper seal: "Sealed for Your Protection." Do not use if seal is broken or missing.

Keep out of reach of children. In case of overdose, contact a physician or Poison Control Center right away.

DIRECTONS:

1-10 drops under the tongue, 2 times a day or as directed by a health professional. Consult a physician for use in children under 12 years of age.

HOMEOPATHIC INDICATIONS:

For the temporary relief of symptoms related to illness and infections such as cold and flu.**

**These statements are based upon homeopathic principles. They have not been reviewed by the Food and Drug Administration.

INACTIVE INGREDIENTS:

Demineralized Water, 25% Ethanol

QUESTIONS:

Dist. By: Deseret Biologicals, Inc.

469 W. Parkland Drive

Sandy, UT 84070 www.desbio.com

PACKAGE LABEL DISPLAY:

DESBIO

NDC 43742-1602-1

HOMEOPATHIC

BIO GALIUM

PHASE

1 FL OZ (30 ml)